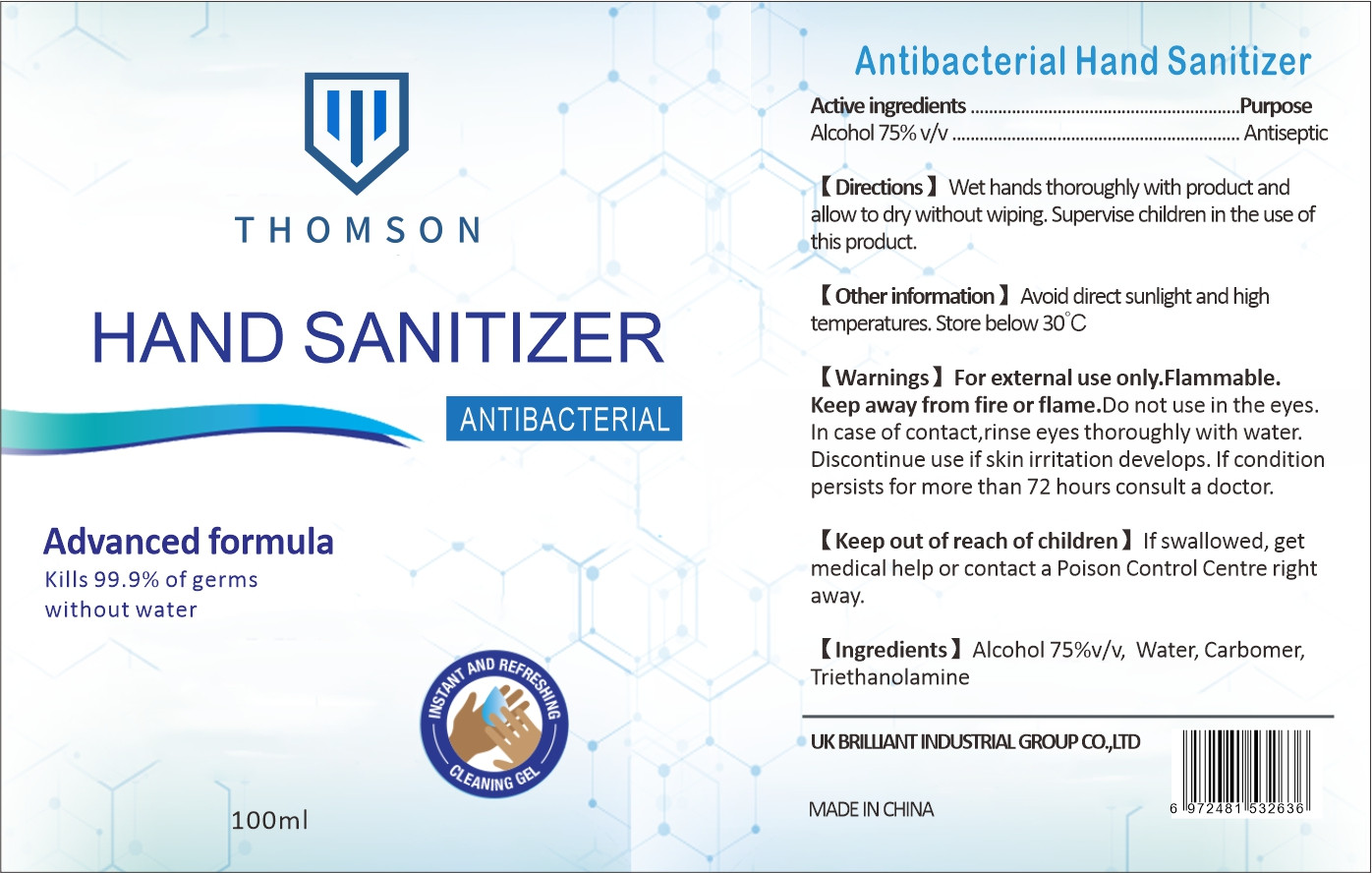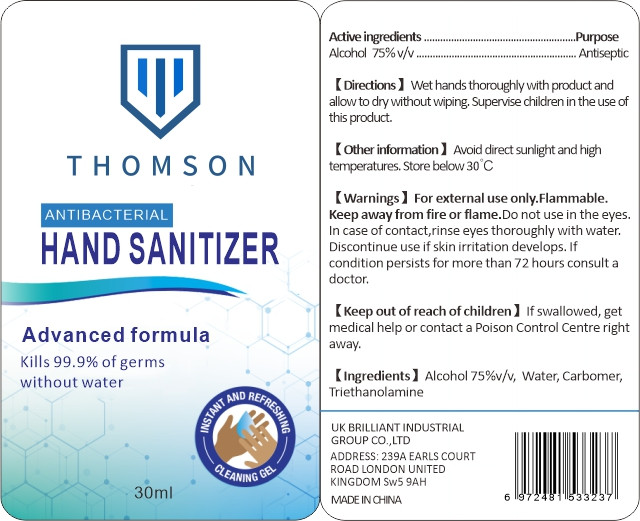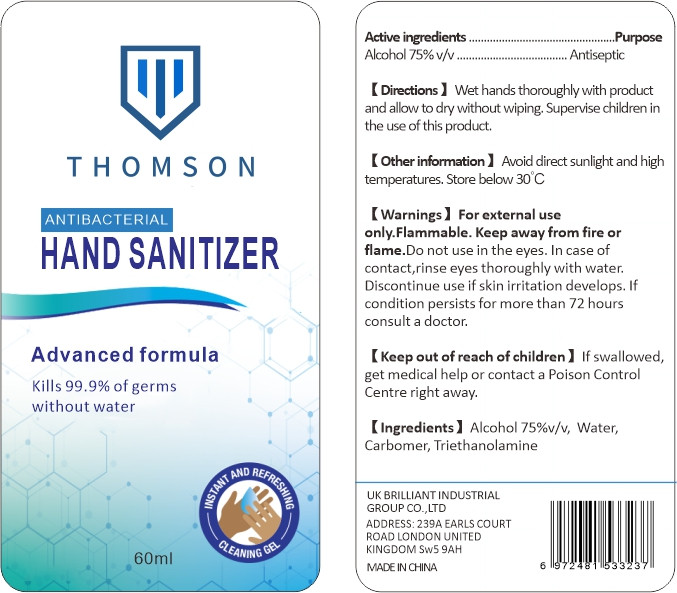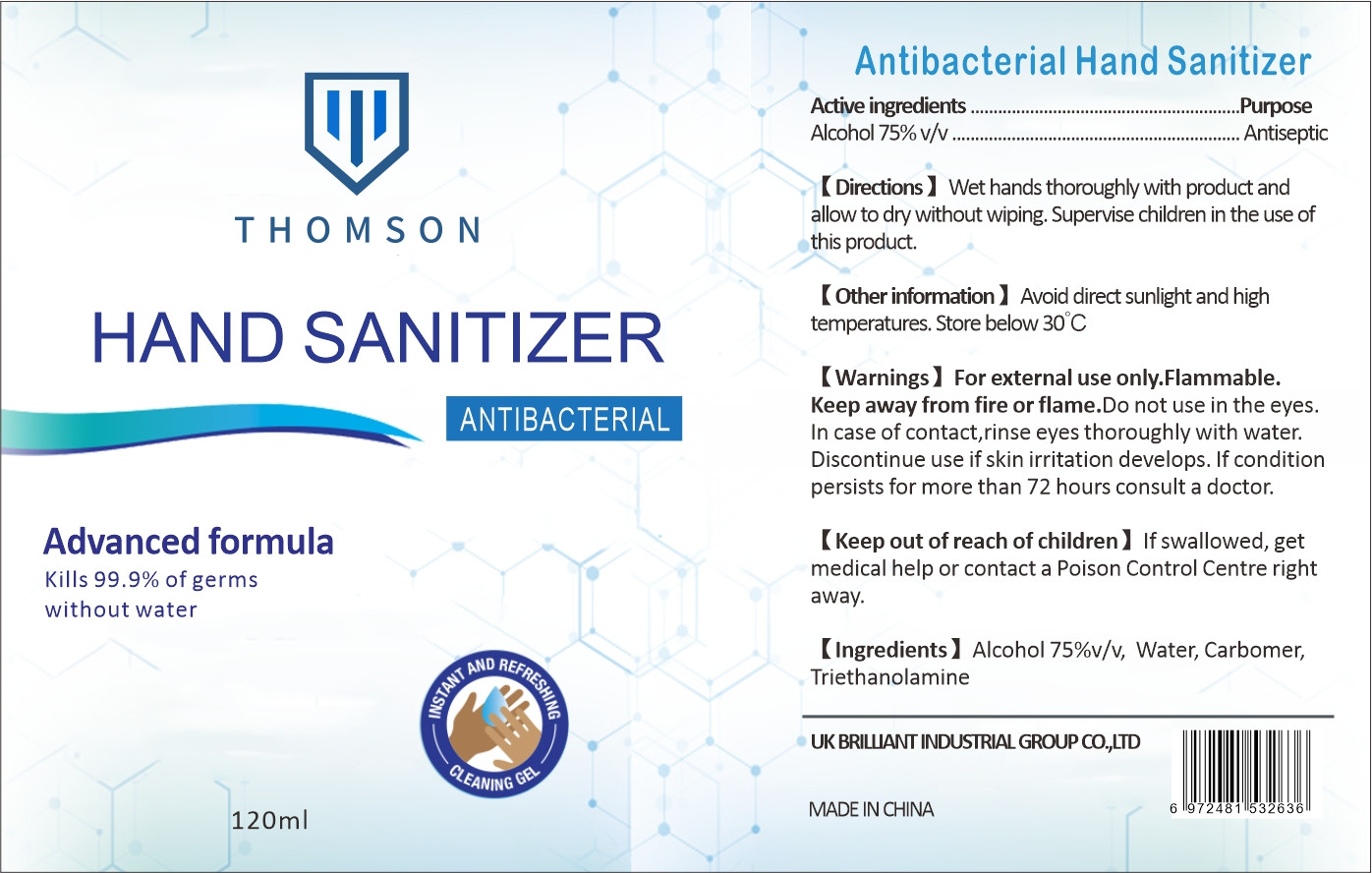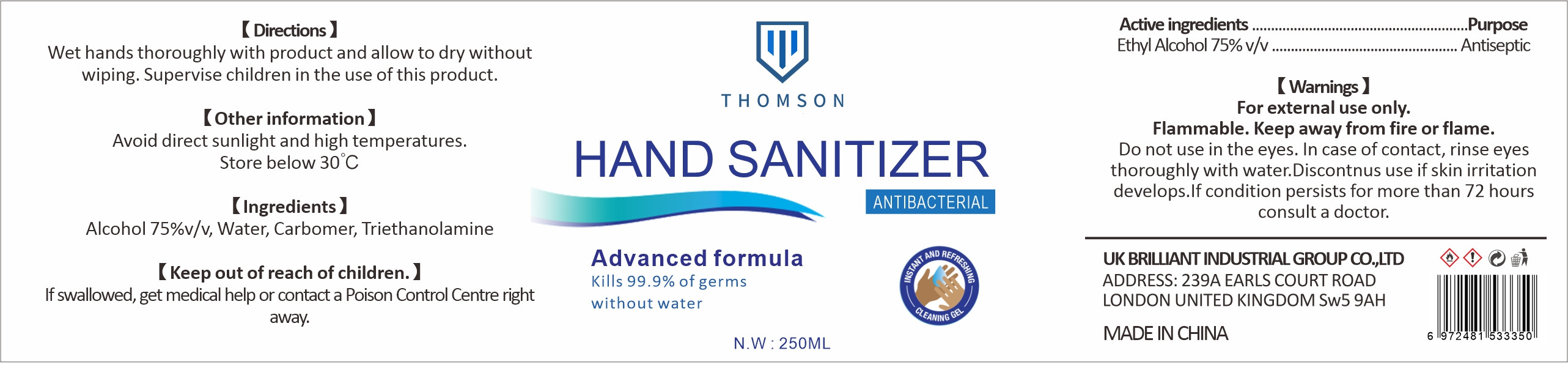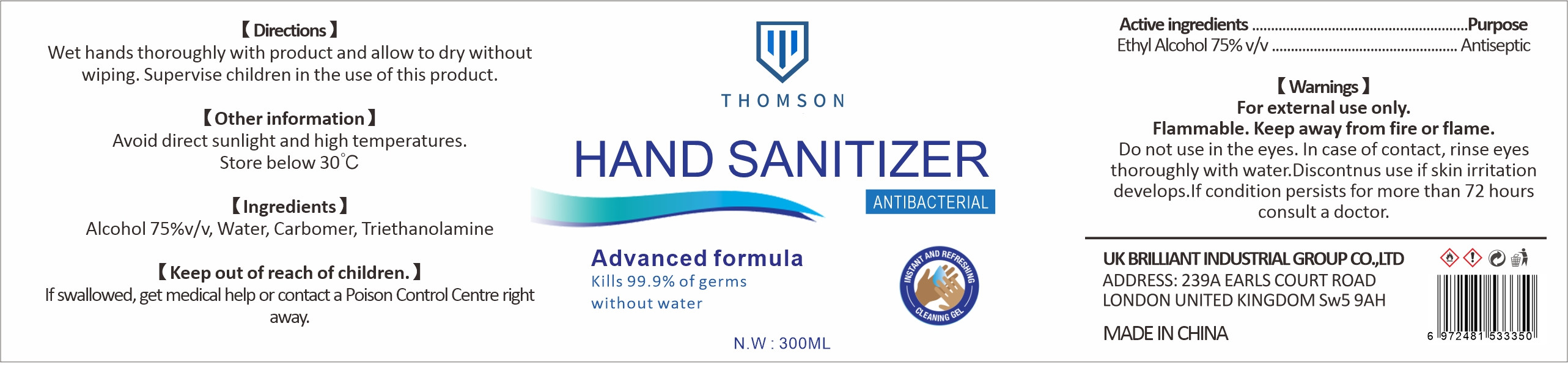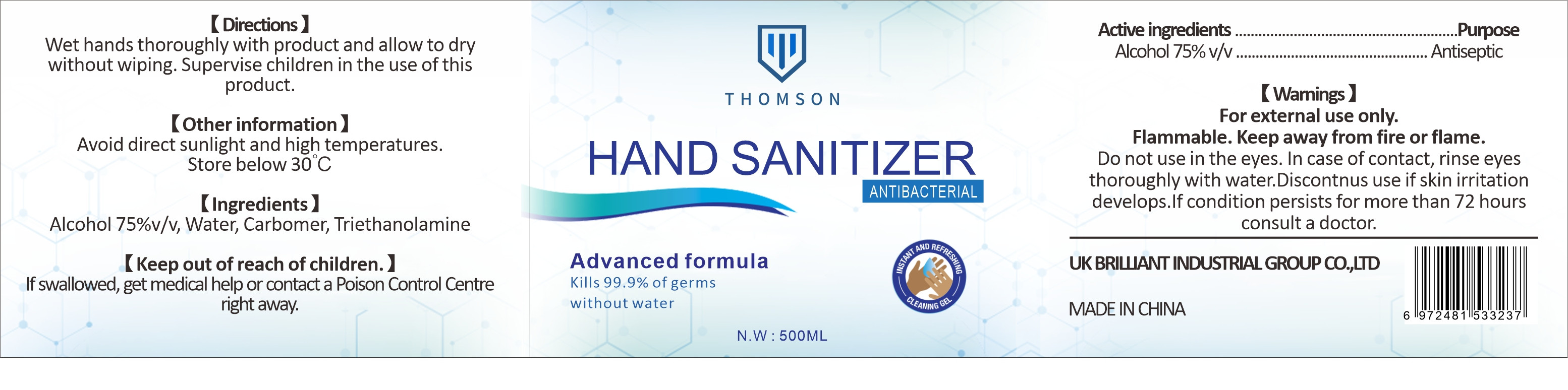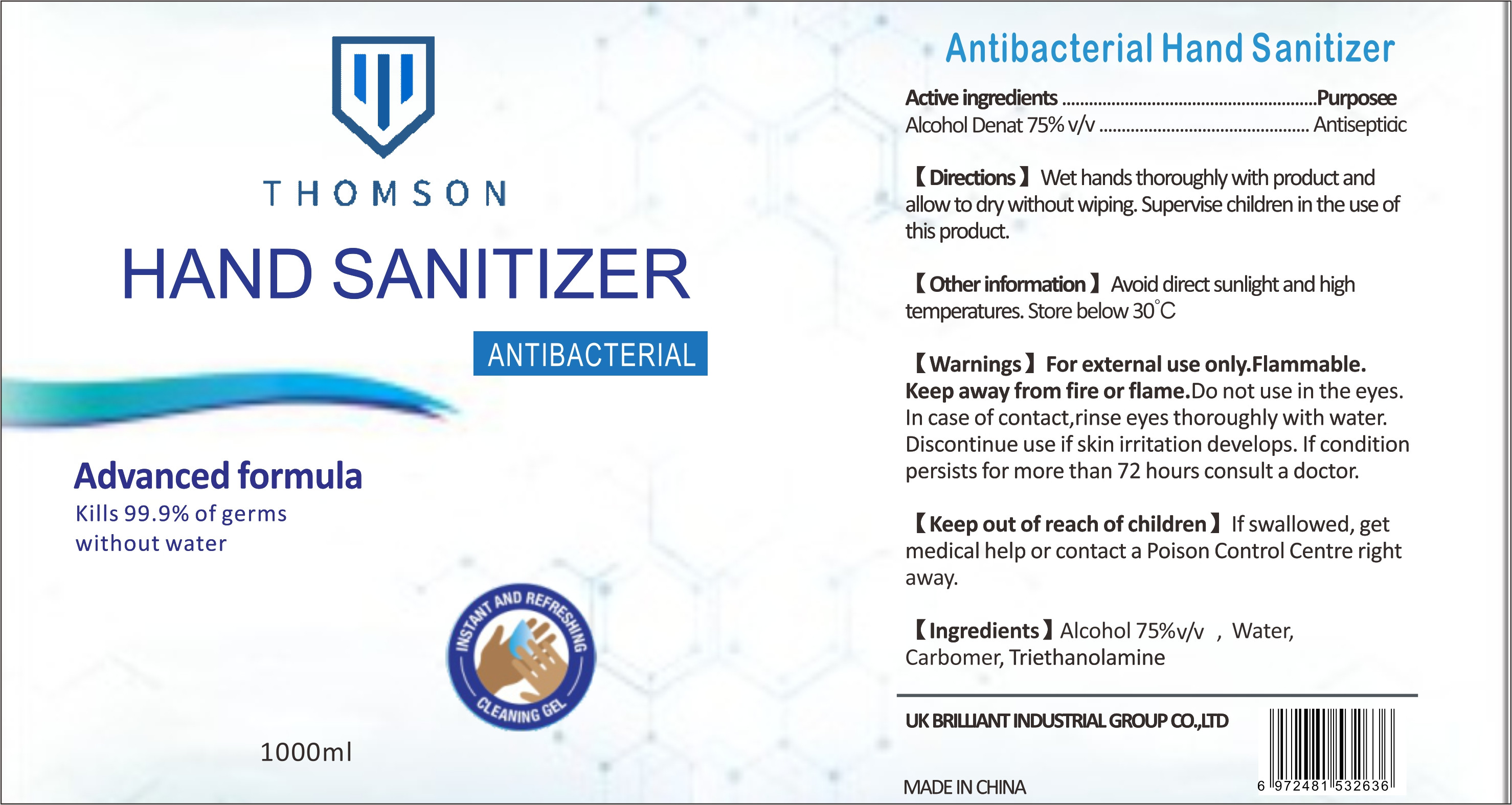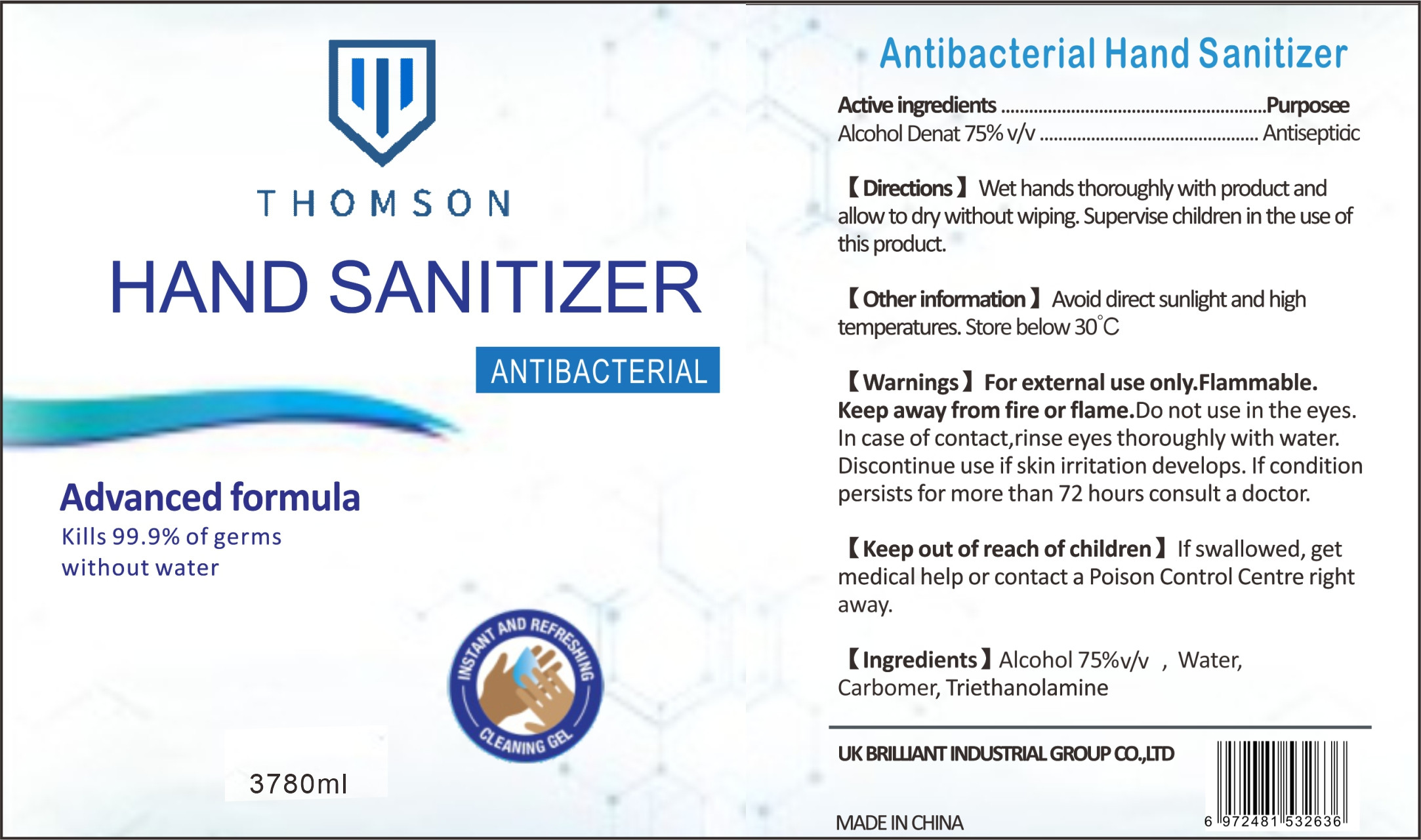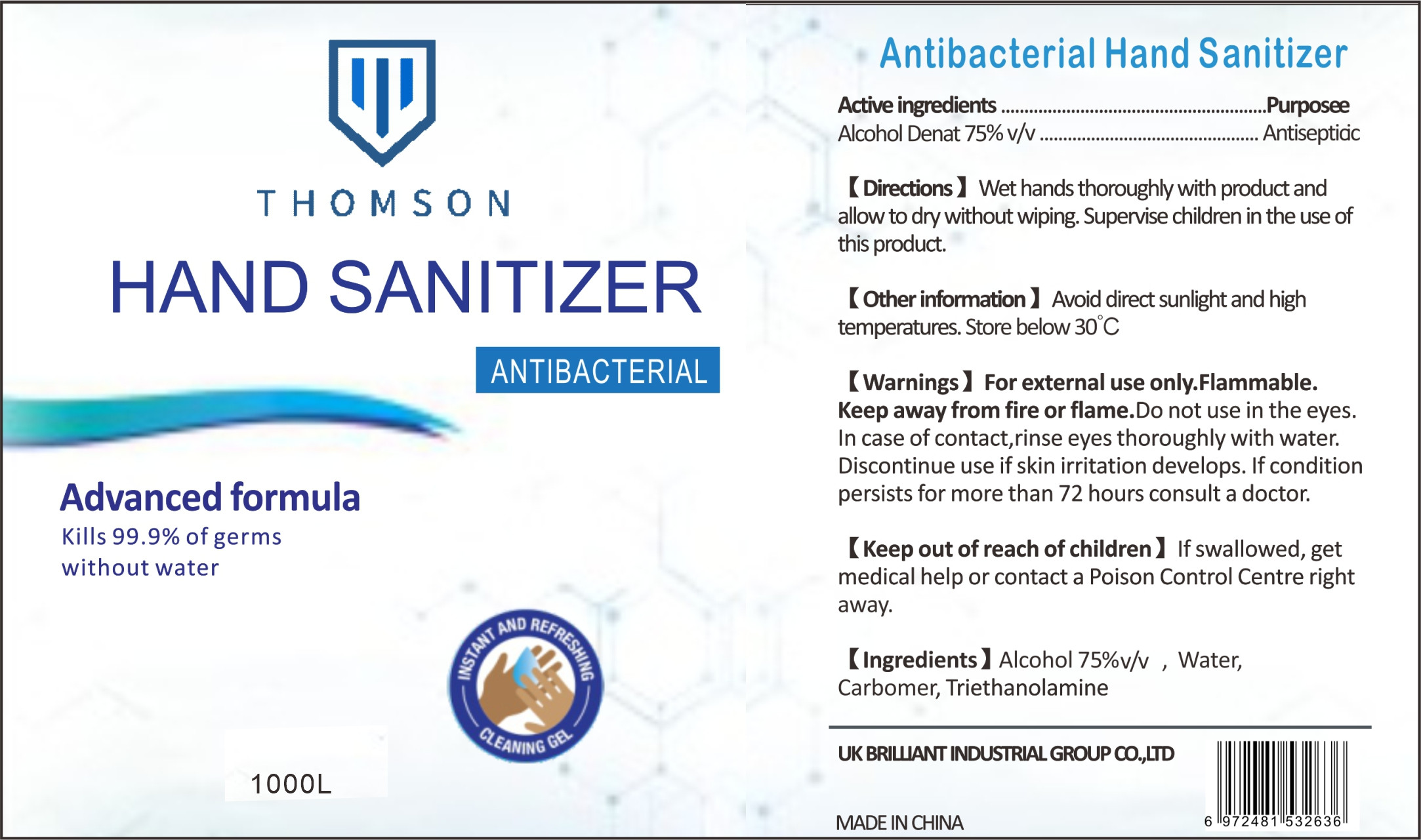 DRUG LABEL: Antibacterial Instant Hand Sanitizer
NDC: 55467-015 | Form: GEL
Manufacturer: INTENTLY (GUANGZHOU) BIOTECHNOLOGY CO., LTD.
Category: otc | Type: HUMAN OTC DRUG LABEL
Date: 20200616

ACTIVE INGREDIENTS: ALCOHOL 75 mL/100 mL
INACTIVE INGREDIENTS: WATER; CARBOMER HOMOPOLYMER, UNSPECIFIED TYPE; TROLAMINE

DOSAGE AND ADMINISTRATION

Avoid direct sunlight and high temperatures. Store below 30°C

INACTIVE INGREDIENT

Water、Carbomer、Triethanolamine

INDICATIONS AND USAGE

Wet hands thoroughly with product and allow to dry without wiping. Supervise children in the use of this product.

ACTIVE INGREDIENT

Alcohol

keep out of reach of children

PURPOSE

Disinfection
Sterilization
No Rinseing

WARNINGS

For external use only.Flammable.Keep away from fire or flame.Do not use in the eyes.In case of contact,rinse eyes thoroughly with water.Discontinue use if skin irritation develops. If condition persists for more than 72 hours consult a doctor.